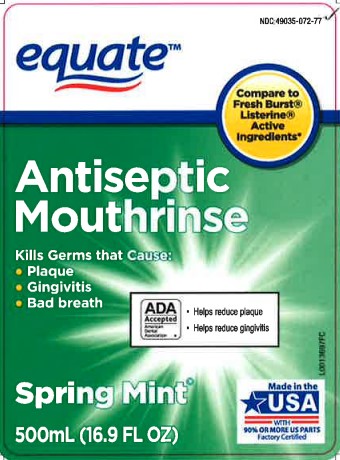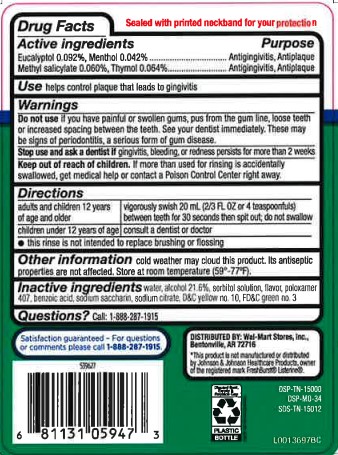 DRUG LABEL: Antiseptic Mouthrinse
NDC: 49035-072 | Form: MOUTHWASH
Manufacturer: Walmart Inc.
Category: otc | Type: HUMAN OTC DRUG LABEL
Date: 20260227

ACTIVE INGREDIENTS: EUCALYPTOL 0.92 mg/1 mL; MENTHOL 0.42 mg/1 mL; METHYL SALICYLATE 0.6 mg/1 mL; THYMOL 0.64 mg/1 mL
INACTIVE INGREDIENTS: WATER; ALCOHOL; SORBITOL; POLOXAMER 407; BENZOIC ACID; SACCHARIN SODIUM; SODIUM CITRATE; D&C YELLOW NO. 10; FD&C GREEN NO. 3

Equate 072.003/072AL rev 2
Spring Mint Antiseptic Mouthrinse

TEP

Sealed with printed neckband for your protection

Active ingredients

Eucalyptol 0.092%, Menthol 0.042%, Methyl sailcylate 0.060%, Thymol 0.064%

Purpose

Antigingivitis, Antiplaque

Use

helps control plaque that leads to gingivitis

Warnings

For this product

Do not use if

you have painful or swollen gums, pus from the gum line, loose teeth or increased spacing between the teeth. See your dentist immediately. These may be signs of periodontitis, a serious form of gum disease.

Stop use and ask a dentist if

gingivitis, bleeding, or rednss persists for more than 2 weeks

Keep out of reach of children

If more than used for rinsing is accidentally swallowed, get medical help or contact a Poison Control Center right away.

Directions

adults and children under 12 years if age and older - vigorously swish 20 ml (2/3 FL OZ or 4 teaspoonfuls) between teeth for 30 seconds then spit out; do not swallow

children under 12 years of age - consult a dentist or doctor

- this rinse is not intended to replace brushing or flossing

Other information

cold weather may cloud this product. Its antiseptic propeties are not affected. Store at room temperature (59° -77° F).

Inactive ingredients

water, alcohol 21.6 %, sorbitol solution, flavor, poloxamer 407, benzoic acid, sodium saccharin, sodium citrate, D&C yellow 10, FD&C green 3

Satisfaction guaranteed

- Or we'll replace it or give you your money back. For questions or comments or to report an undesired reaction or side effect, please call 1-888-287-1915.

Adverse Reactions Section

DISTRIBUTED BY: Wal-Mart Stores, Inc., Bentonville, AR 72716

*This product is not manufactured or distributed by Johnson & Johnson Healthcare Products, owner of the registered mark FreshBurst Listerine.

how2recycle.info

Discard Seal, Empty & Replace Cap

Plastic Bottle

DSP-TN-15000

DSP-MO-34

SDS-TN-15012

Principal Display Panel

NDC: 49035-072-77

equate™

Compare to FreshBurst®Listerine®Active Ingredients*

Antiseptic Mouthrinse

Kills Germs that Cause:

- Plaque
- Gingivitis
- Bad breath

ADA Accepted

American Dental Association

- Helps reduce plaque
- Helps reduce gingivitis

Spring Mint

Made in the USA

with 90% OR MORE US PARTS

Factory Certified

500mL (16.9 FL OZ)